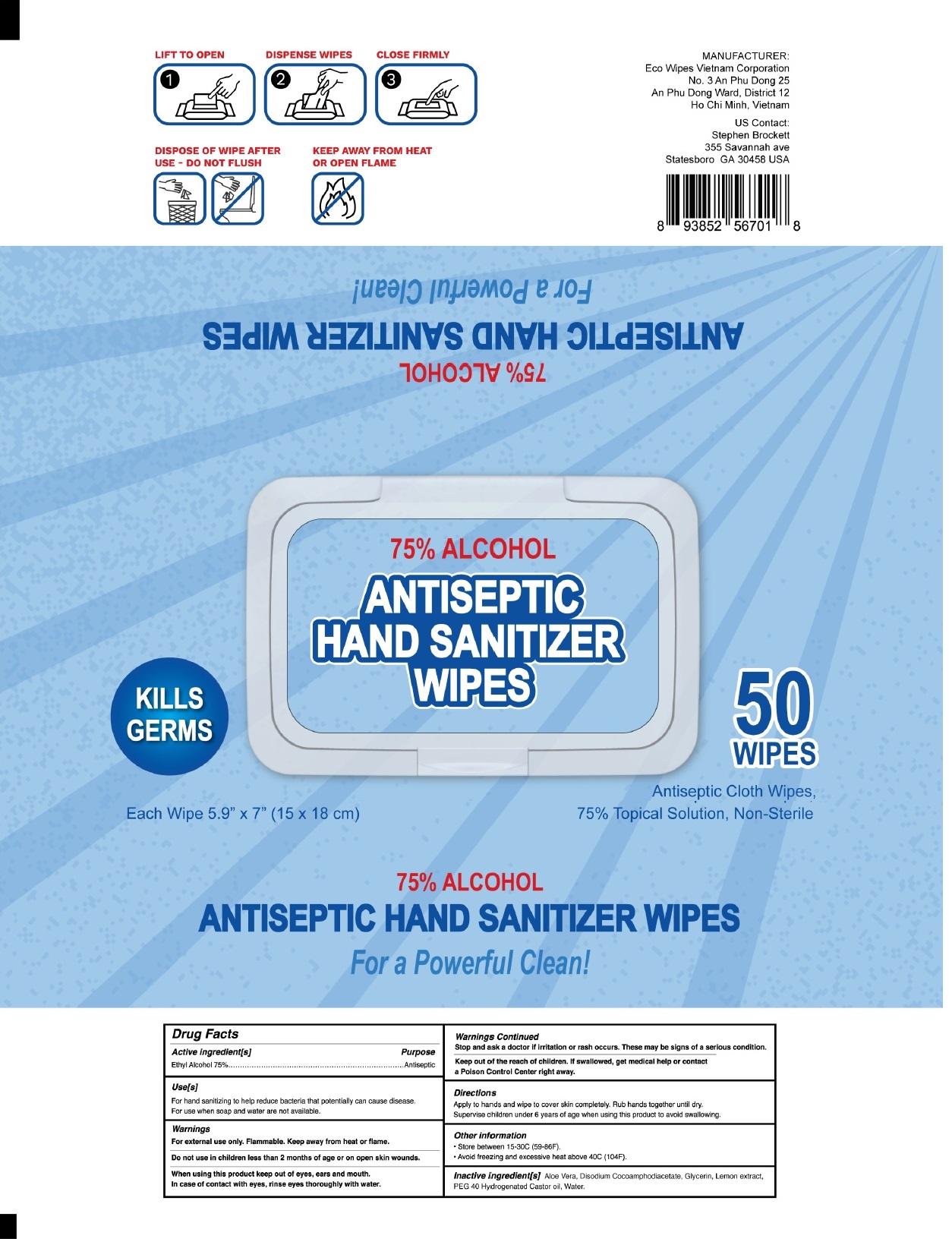 DRUG LABEL: ANTISEPTIC HAND SANITIZER WIPES
NDC: 78898-475 | Form: CLOTH
Manufacturer: Eco Wipes Vietnam Corporation
Category: otc | Type: HUMAN OTC DRUG LABEL
Date: 20200817

ACTIVE INGREDIENTS: ALCOHOL 75 mL/100 mL
INACTIVE INGREDIENTS: ALOE VERA LEAF; DISODIUM COCOAMPHODIACETATE; GLYCERIN; LEMON; POLYOXYL 40 HYDROGENATED CASTOR OIL; WATER

ANTISEPTIC HAND SANITIZER WIPES

Active ingredient[s]

Ethyl Alcohol 75%

Purpose

Antiseptic

Use[s]

For hand sanitizing to help reduce bacteria that potentially can cause disease. For use when soap and water are not available.

Warnings

For external use only. Flammable. Keep away from heat or flame.

Do not use in children less than 2 months of age or on open skin wounds.

When using this product keep out of eyes, ears, and mouth.

In case of contact with eyes, rinse thoroughly with water.

Stop use and ask a doctor if irritation or rash occurs. These may be signs of a serious condition.

Keep out of reach of children. If swallowed, get medical help or contact a Poison Control Center right away.

Directions

Apply to hands and wipe to cover skin completely. Rub hands together until dry.

Supervise children under 6 years of age when using this product to avoid swallowing.

Other information

• Store between 15-30C (59-86F).

• Avoid freezing and excessive heat above 40C (104F).

Inactive ingredient[s] Aloe Vera, Disodium Cocoamphodiacetate, Glycerin, Lemon extract, PEG 40 Hydrogenated Castor Oil, Water.

KILLS GERMS

Antiseptic Cloth Wipes, 75% Topical Solution, Non-Sterile

Each Wipe 5.9” X 7" (15 x 18 cm)

For a Powerful Clean!

1. LIFT TO OPEN

2. DISPENSE WIPES

3. CLOSE FIRMLY

DISPOSE OF WIPE AFTER USE - DO NOT FLUSH

KEEP AWAY FROM HEAT OR OPEN FLAME

MANUFACTURER:

Eco Wipes Vietnam Corporation

No.3 An Phu Dong 25

An Phu Dong Ward, District 12

Ho Chi Minh, Vietnam

US Contact:

Stephen Brockett

355 Savannah ave

Statesboro GA 30458 USA